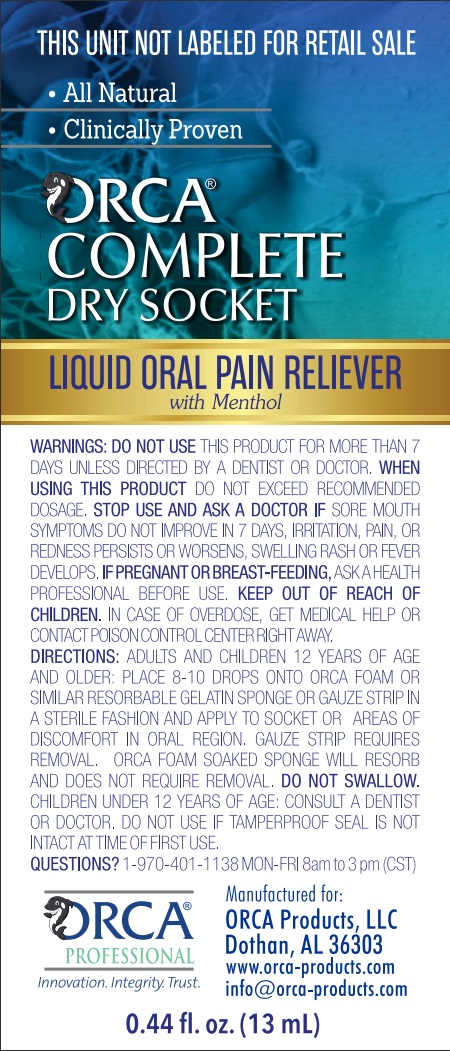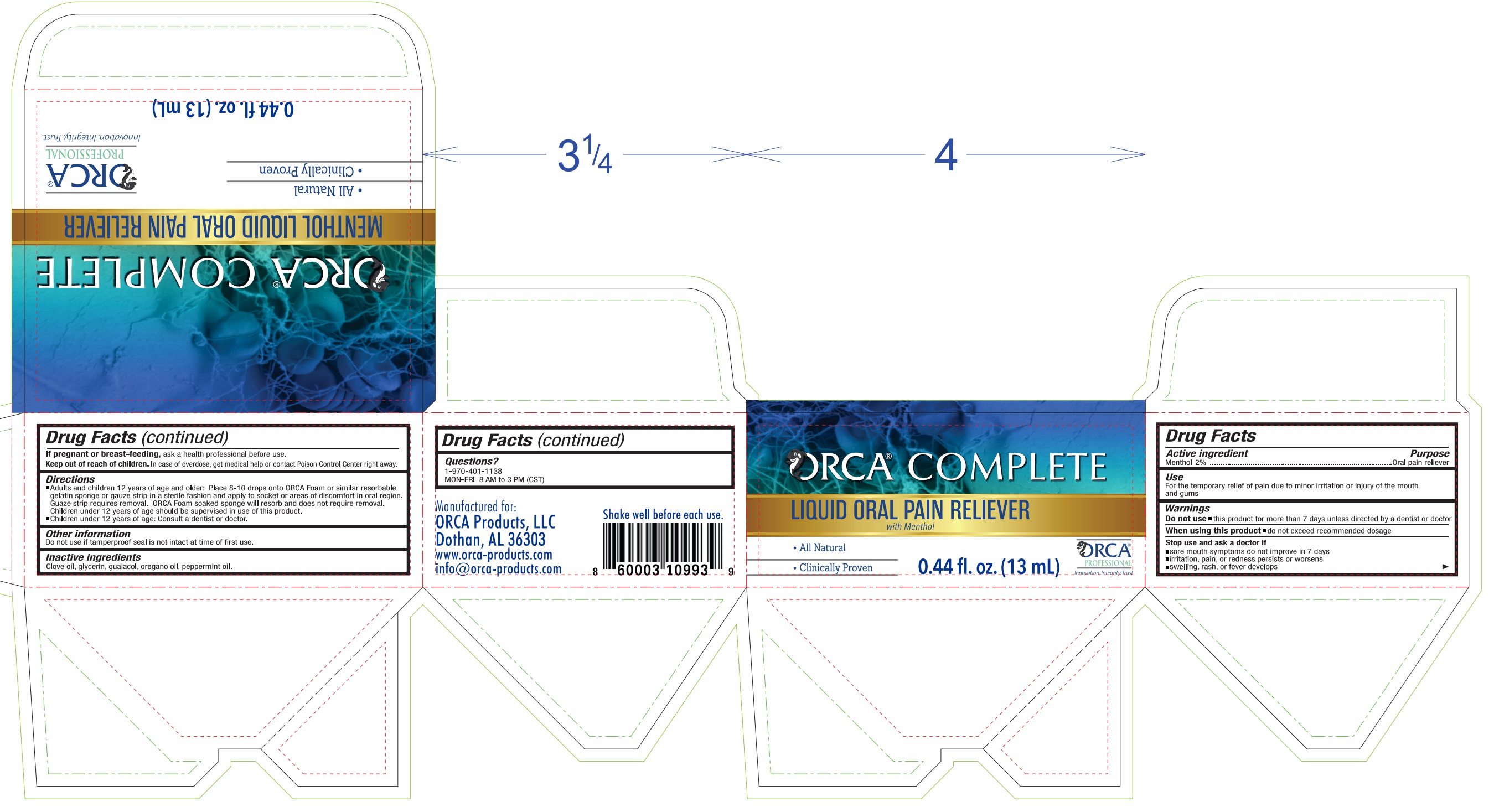 DRUG LABEL: ORCA Complete Menthol Pain Reliever
NDC: 82939-000 | Form: LIQUID
Manufacturer: ORCA Products, LLC
Category: otc | Type: HUMAN OTC DRUG LABEL
Date: 20231208

ACTIVE INGREDIENTS: MENTHOL, UNSPECIFIED FORM 20 mg/1 mL
INACTIVE INGREDIENTS: CLOVE OIL; GLYCERIN; GUAIACOL; OREGANO LEAF OIL; PEPPERMINT OIL

ORCA Complete Menthol Oral Pain Reliever

Active ingredient

Menthol 2%

Purpose

oral pain reliever

Use

- for the temporary relief of pain due to minor irritation or injury of the mouth and gums

Warnings

Do not use

- this product for more than 7 days unless directed by a dentist or doctor.

When using this product

- do not exceed recommended dosage.

Stop use and ask a doctor if

- sore mouth symptoms do not improve in 7 days
- irritation, pain, or redness persists or worsens
- swelling, rash, or fever develops

If pregnant or breast-feeding,

ask a health professional before use.

Keep out of reach of children.

In case of overdose, get medical help or contact Poison Control Center right away.

Directions

- Adults and children 12 years of age and older: Place 8-10 drops onto ORCA Foam or similar resorbable gelatin sponge or gauze strip in a sterile fashion and apply to areas of discomfort in oral region. Guaze strip requires removal. Orca Foam soaked sponge will resorb and does not require removal.
- Children under 12 years of age should be supervised in use of this product.
- Children under 12 years of age: Consult a dentist or doctor.

Other information

- Do not use if tamperproof seal is not intact at time of first use.

Inactive ingredients

Clove oil, glycerin, guaiacol, oregano oil, peppermint oil.

Questions?

1-970-401-1138 MON-FRI 8 AM to 3 PM (CST)